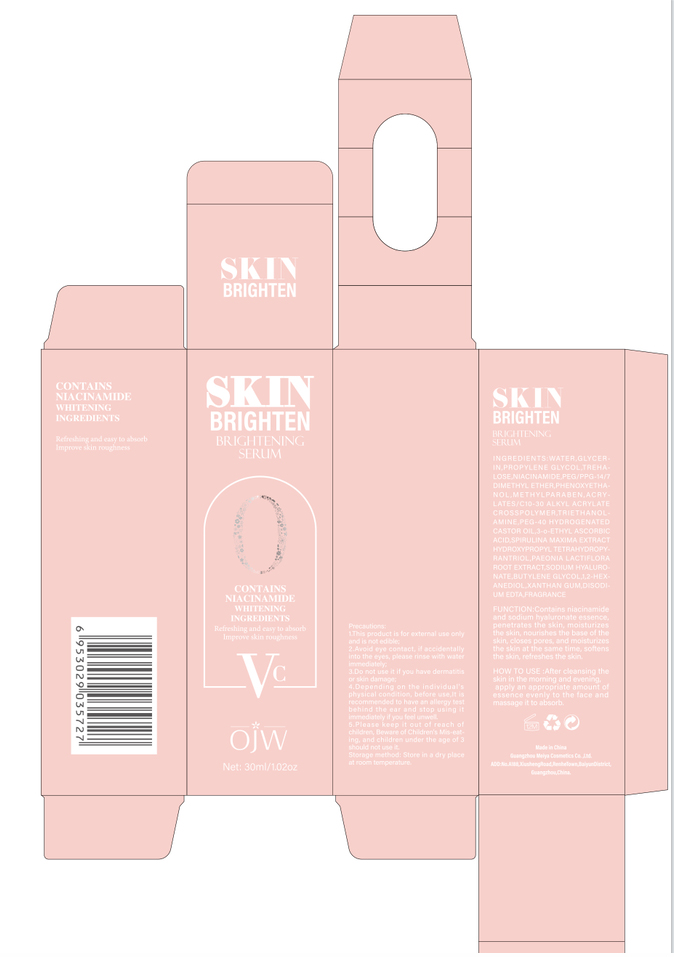 DRUG LABEL: Brightening
NDC: 84673-013 | Form: EMULSION
Manufacturer: Guangzhou Meiya Cosmetics Co. ,Ltd.
Category: otc | Type: HUMAN OTC DRUG LABEL
Date: 20241002

ACTIVE INGREDIENTS: NIACINAMIDE 30 mg/1 mL
INACTIVE INGREDIENTS: WATER 84.909 mg/1 mL; GLYCERIN 5 mg/1 mL; PEG/PPG-14/7 DIMETHYL ETHER 1 mg/1 mL; PHENOXYETHANOL 0.5 mg/1 mL; METHYLPARABEN 0.35 mg/1 mL; 3-O-ETHYL ASCORBIC ACID 0.15 mg/1 mL; XANTHAN GUM 0.1 mg/1 mL; BUTYLENE GLYCOL 0.0032 mg/1 mL; 1,2-HEXANEDIOL 0.0001 mg/1 mL; HYDROXYPROPYL TETRAHYDROPYRANTRIOL 0.001 mg/1 mL; TREHALOSE 2 mg/1 mL

PURPOSE

Function:Contains niacinamide and sodium hyaluronate essence, penetrates the skin, moisturizes the skin, nourishes the base of the skin, closes pores, and moisturizes the skin at the same time, softens the skin, refreshes the skin.

INDICATIONS AND USAGE

HOW TO USE :After cleansing the skin in the morning and evening,

apply an appropriate amount of essence evenly to the face and massage it to absorb.

WARNINGS

1. This product is for external use only and is not edible;

2. Avoid eye contact, if accidentally into the eyes, please rinse with water immediately;

3. Do not use it if you have dermatitis or skin damage;

4. Depending on the individual's physical condition, before use,It is recommended to have an allergy test behind the ear and stop using it immediately if you feel unwell.

5. Please keep it out of reach of children, Beware of Children's Mis-eating, and children under the age of 3 should not use it.

STOP USE

1. Avoid eye contact, if accidentally into the eyes, please rinse with water immediately;

2. Do not use it if you have dermatitis or skin damage;

3. Depending on the individual's physical condition, before use,It is recommended to have an allergy test behind the ear and stop using it immediately if you feel unwell.

DO NOT USE

1. Avoid eye contact, if accidentally into the eyes, please rinse with water immediately;

2. Do not use it if you have dermatitis or skin damage;

3. Depending on the individual's physical condition, before use,It is recommended to have an allergy test behind the ear and stop using it immediately if you feel unwell.

KEEP OUT OF REACH OF CHILDREN

Please keep it out of reach of children, Beware of Children's Mis-eating, and children under the age of 3 should not use it.

WHEN USING

1. This product is for external use only and is not edible;

2. Avoid eye contact, if accidentally into the eyes, please rinse with water immediately;

3. Do not use it if you have dermatitis or skin damage;

4. Depending on the individual's physical condition, before use,It is recommended to have an allergy test behind the ear and stop using it immediately if you feel unwell.

5. Please keep it out of reach of children, Beware of Children's Mis-eating, and children under the age of 3 should not use it.